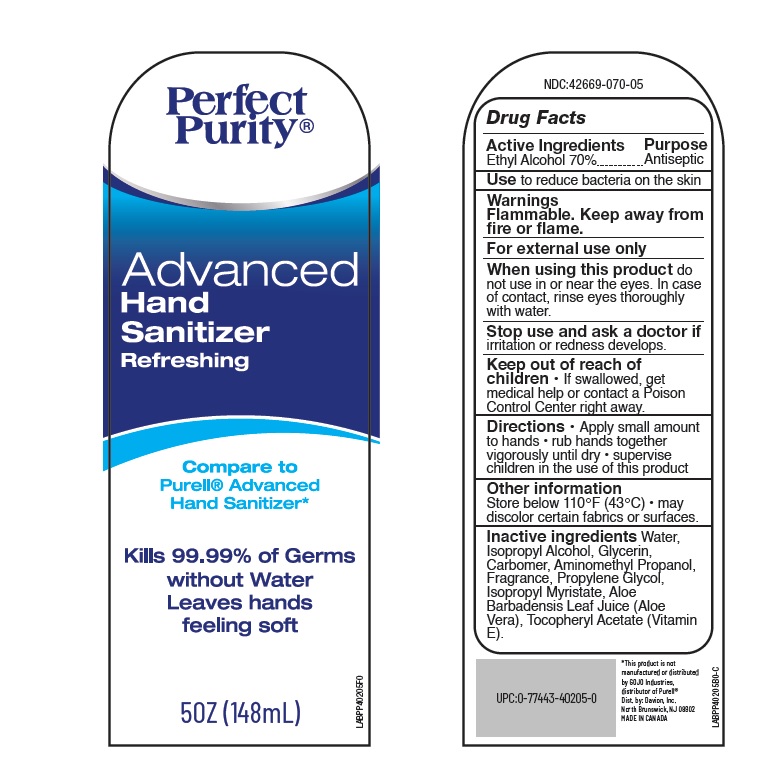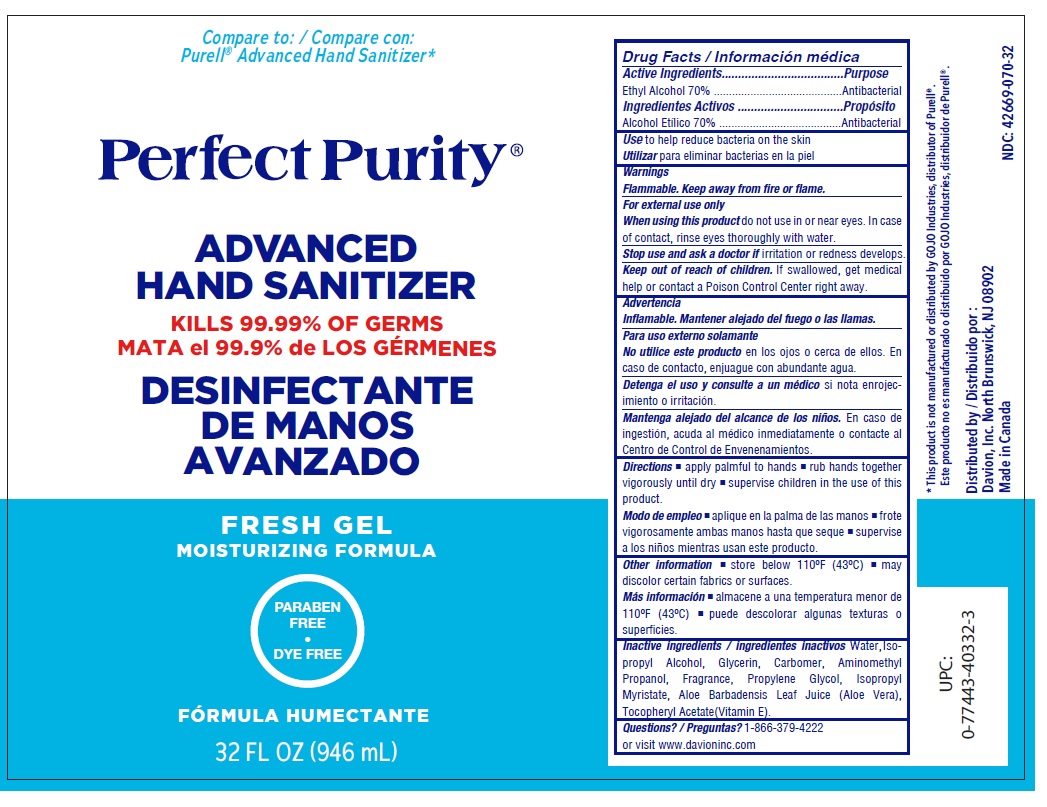 DRUG LABEL: Advanced Hand SanitizerRefreshin
NDC: 42669-070 | Form: LIQUID
Manufacturer: Davion, Inc
Category: otc | Type: HUMAN OTC DRUG LABEL
Date: 20200313

ACTIVE INGREDIENTS: ALCOHOL 70 mL/1 mL
INACTIVE INGREDIENTS: WATER; ISOPROPYL ALCOHOL; GLYCERIN; CARBOMER HOMOPOLYMER, UNSPECIFIED TYPE; AMINOMETHYLPROPANOL; PROPYLENE GLYCOL; ISOPROPYL MYRISTATE; ALOE VERA LEAF; .ALPHA.-TOCOPHEROL ACETATE

Active Ingredient

Ethyl Alcohol 70%

Purpose

Antiseptic

Use

To reduce bacteria on skin

Warnings

Flammable, Keep away from fire or flame.

For external use only.

When using this product

do not use in or near the eyes. In case of contact, rinse eyes thoroughly with water

Stop use and ask a doctor if

irritation or redness develops

Keep out of reach of children

If swallowed, get medical help or contact or contact a Poison Control Center right away

Directions

- Apply small amounts to hands
- rub hands together vigorously until dry
- supervise children in the use of this product

Other information

Store below 110°F (43° C)

may discolor certain fabrics or surfaces

Inactive Ingredients

Water, Isopropyl Alcohol, Glycerin, Carbomer, Aminomethyl Propano, Fragrance, Propylene Glycol, Isopropyl Myristate, Aloe Barbadensis Leaf Juice (Aloe Vera), Tocopheryl Acetate (Vitamin E).

Questions

1-866-379-4222 or visit www.davioninc.com

Principal Display Panel

NDC 42669-070-05

Perfect Purity®

Advanced Hand Sanitizer Refreshing

Compare to Purell® Advanced Hand Sanitizer*

Kills 99.99% of Germs without Water

Leaves hands feeling soft

MOISTURE-RICH

5 oz (148 ml)

NDC 42669-070-32

Perfect Purity®

Advanced Hand Sanitizer Refreshing

Compare to Purell® Advanced Hand Sanitizer*

Kills 99.99% of Germs without Water

FRESH GEL

MOISTURIZING FORMULA

PARABEN FREE

DYE FREE

32 FL OZ (946 mL)